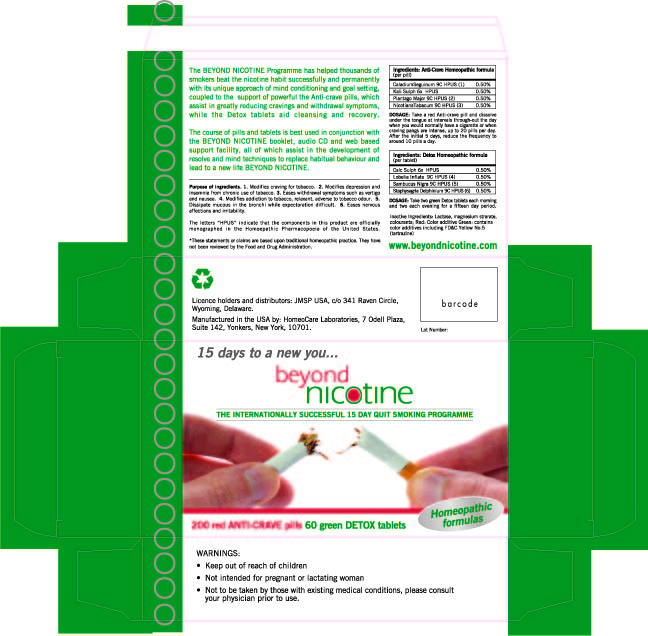 DRUG LABEL: beyond nicotine kit
NDC: 58214-100 | Form: KIT | Route: ORAL
Manufacturer: JMSP USA LLC
Category: homeopathic | Type: HUMAN OTC DRUG LABEL
Date: 20181110

ACTIVE INGREDIENTS: DIEFFENBACHIA SEGUINE 9 [hp_C]/200 1; POTASSIUM SULFATE 6 [hp_X]/200 1; PLANTAGO MAJOR 9 [hp_C]/200 1; TOBACCO LEAF 9 [hp_C]/200 1; CALCIUM SULFATE ANHYDROUS 6 [hp_C]/60 1; ATROPA BELLADONNA 6 [hp_X]/60 1; LOBELIA INFLATA 9 [hp_X]/60 1; SAMBUCUS NIGRA FLOWERING TOP 6 [hp_X]/60 1; DELPHINIUM STAPHISAGRIA SEED 6 [hp_X]/60 1
INACTIVE INGREDIENTS: LACTOSE; MAGNESIUM STEARATE; FD&C YELLOW NO. 5; LACTOSE; MAGNESIUM STEARATE; FD&C YELLOW NO. 5

Beyond Nicotine Quit Smoking Kit

Ingredients: Detox Homeopathic formula (per tablet)

Calc Sulph 6x HPUS 0.50%

Lobelia Inflata 9c HPUS (4) 0.50%

Sambucus Nigra 9c HPUS (5) 0.50%

Staphysagria Delphinium 9c HPUS (6) 0.50%

Purpose of ingredients:

1. Modifies craving for tobacco. 2. Modifies depression and insomnia from chronic use of tobacco. 3. Eases withdrawal symptoms such as vertigo and nausea, 4. Modifies addiction to tobacco, relaxant, adverse to tobacco odour. 5. Dissipate mucous in the bronchi while expectoration difficult. 6. Eases nervous affections and irritability.

The letters "HPUS" indicate that the components in this product are officially monographed in the Homeopathic Pharmacopoeia of the United States.

*These statements or claims are based upon traditional homeopathic practice. They have not been reviewed by the Food and Drug Administration.

Warnings:

- Keep out of reach of children
- Not intended for pregnant or lactating women
- Not to be taken by those with existing medical conditions, please consult your prior to use.

Warnings:

- Keep out of reach of children
- Not intended for pregnant or lactating women
- Not to be taken by those with existing medical conditions, please consult your physician prior to use.

Indications and Usage:

Anti-crave pills (each pill contains: Caladium Seguinum 9C HPUS1, Kali Sulph 6x HPUS, Plantago Major 9C HPUS2, Nicotiana Tabacum 9C HPUS3)
Take a red Anti-crave pill and dissolve under the tongue at intervals through-out the day when you would normally have a cigarette or when craving pangs are intense, you can take up to 20 pills per day. After the initial 5 days, reduce the frequency to around 10 pills a day.
Detox tablets (each tablet contains: Calc Sulph 6x HPUS, Lobelia Inflata 9C HPUS4, Sambucus Nigra 9C HPUS5, and Staphysagria Delphinium 9C HPUS6) Take two green Detox tablets each morning and two each evening for a fifteen day period.

Inactive Ingredients:

Lactose, magnesium strarate, colourants; Red: Color additive. Green: contains color additives including FD&C. Yellow No.5 (tartrazine)

Ingredients: Anti-Crave Homeopathic formula (per pill)

Caladium Seguinum 9c HPUS (1) 0.50%

Kali Sulph 6x HPUS 0.50%

Plantago Major 9c HPUS (2)0.50%

Nicotiana Tabacum 9c HPUS (3) 0.50%

WARNINGS:

1. Modifies craving for tobacco. 2. Modifies depression and insomnia from chronic use of tobacco. 3. Eases withdrawal symptoms such as vertigo and nausea. 4. Modifies addiction to tobacco, relaxant, adverse to tobacco odour. 5. Dissipate mucous in the bronchi while expectoration difficult. 6. Eases nervous affections and irritability.

*These statements or claims are based upon traditional homeopathic practice. They have not been reviewed by the Food and Drug Administration.

Warnings:

Keep out of reach of children.
Not intended for pregnant or lactating woman
Not to be taken by those with existing medical conditions,
please consult your physician prior to use.

Directions for use:

Anti-crave pills (each pill contains: Caladium Seguinum 9C HPUS1, Kali Sulph 6x HPUS, Plantago Major 9C HPUS2, Nicotiana Tabacum 9C HPUS3)
Take a red Anti-crave pill and dissolve under the tongue at intervals through-out the day when you would normally have a cigarette or when craving pangs are intense, you can take up to 20 pills per day. After the initial 5 days, reduce the frequency to around 10 pills a day.
Detox tablets (each tablet contains: Calc Sulph 6x HPUS, Lobelia Inflata 9C HPUS4, Sambucus Nigra 9C HPUS5, and Staphysagria Delphinium 9C HPUS6) Take two green Detox tablets each morning and two each evening for a fifteen day period.

Inactive Ingredients:

Lactose, magnesium strarate, colourants; Red: Color additive. Green: contains color additives including FD&C. Yellow No.5 (tartrazine)

QUESTIONS

www.beyondnicotine.com

Beyond Nicotine Carton The Internationally Successful 15 Day Quit Smoking Programme BeyondNicotine.jpg

15 days to a new you...

beyond nicotine

THE INTERNATIONALLY SUCCESSFUL 15 DAY QUIT SMOKING PROGRAMME

BeyondNicotine.jpg